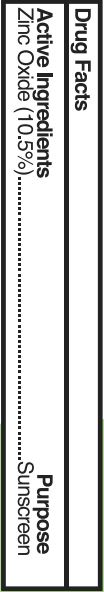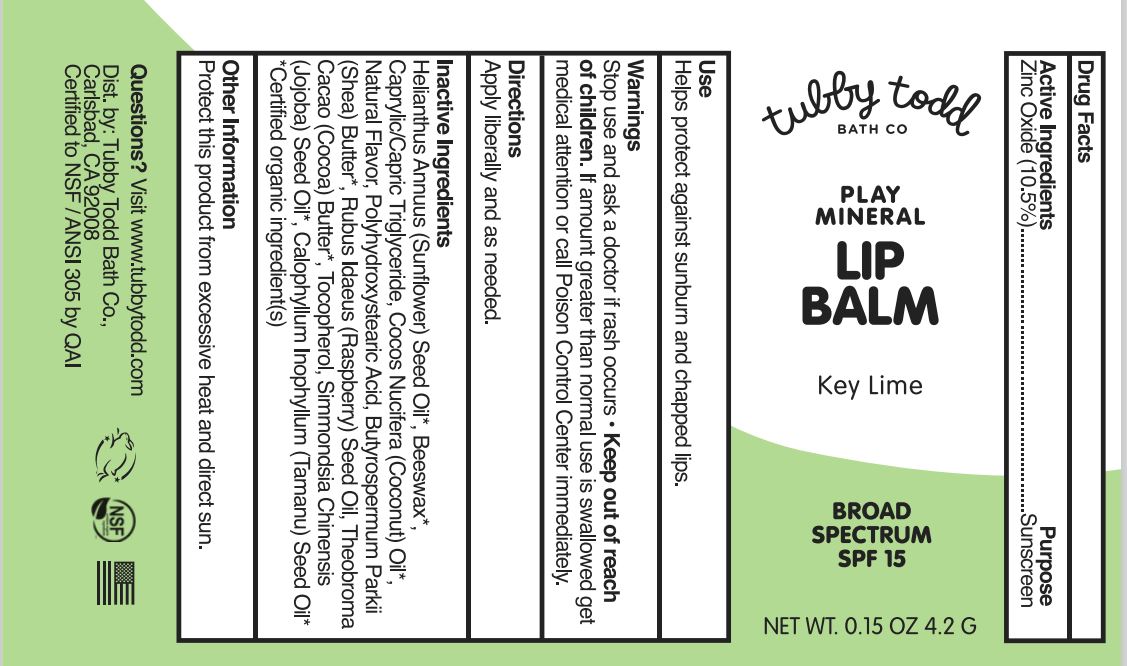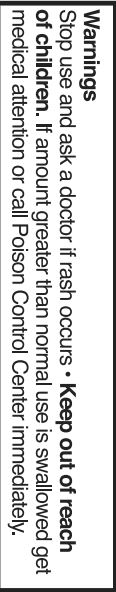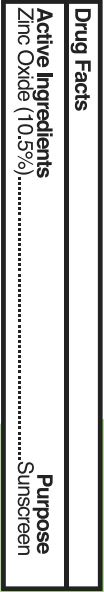 DRUG LABEL: SPF 15 Lip Balm Key Lime
NDC: 62932-251 | Form: STICK
Manufacturer: Private Label Select Ltd CO
Category: otc | Type: HUMAN OTC DRUG LABEL
Date: 20201231

ACTIVE INGREDIENTS: ZINC OXIDE 10 g/100 g
INACTIVE INGREDIENTS: SUNFLOWER OIL; SHEA BUTTER; .DELTA.-TOCOPHEROL; COCONUT OIL; WHITE WAX; MEDIUM-CHAIN TRIGLYCERIDES; RASPBERRY SEED OIL; COCOA BUTTER; .ALPHA.-TOCOPHEROL, D-; .BETA.-TOCOPHEROL; JOJOBA OIL; TAMANU OIL; POLYHYDROXYSTEARIC ACID (2300 MW); .GAMMA.-TOCOPHEROL; POLYHYDROXYSTEARIC ACID STEARATE

Tubby Todd Play Mineral Lip Balm, Key Lime